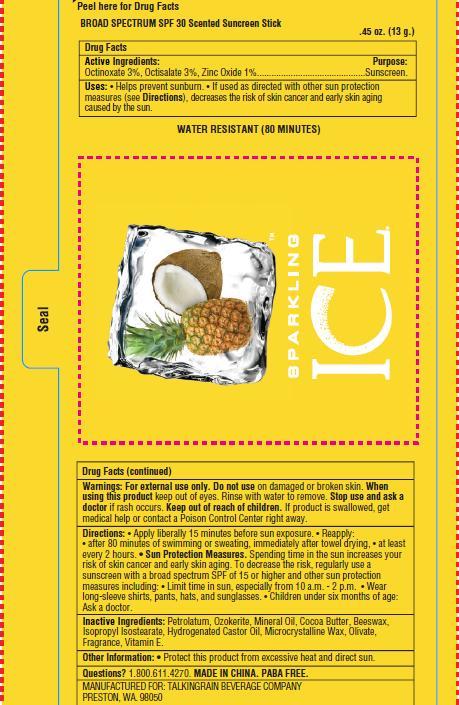 DRUG LABEL:  SUNSCREEN STICK
NDC: 51414-900 | Form: SPRAY
Manufacturer: Yuyao Jessie Commodity Co.,Ltd.
Category: otc | Type: HUMAN OTC DRUG LABEL
Date: 20140508

ACTIVE INGREDIENTS: Octinoxate 3 g/100 g; ZINC OXIDE 1 g/100 g; Octisalate 3 g/100 g
INACTIVE INGREDIENTS: Petrolatum; Mineral oil; Cocoa butter; Isopropyl isostearate; Hydrogenated castor oil; Microcrystalline wax; DECYL OLIVATE; 1.ALPHA.,24S-DIHYDROXYVITAMIN D2

SUNSCREEN STICK

Active Ingredient

Octinoxate 3%, Octisalate 3%, Zinc Oxide 1%

Purpose

Sunscreen

Use

• Helps prevent sunburn. • If used as directed with other sun protection
measures (see Directions), decreases the risk of skin cancer and early skin aging
caused by the sun.

WARNINGS

For external use only. Do not use on damaged or broken skin. When
using this product keep out of eyes. Rinse with water to remove. Stop use and ask a
doctor if rash occurs. Keep out of reach of children. If product is swallowed, get
medical help or contact a Poison Control Center right away.

Keep out of reach of children. If product is swallowed, get
medical help or contact a Poison Control Center right away.

Directions

• Apply liberally 15 minutes before sun exposure. • Reapply:
• after 80 minutes of swimming or sweating, immediately after towel drying, • at least
every 2 hours. • Sun Protection Measures. Spending time in the sun increases your
risk of skin cancer and early skin aging. To decrease the risk, regularly use a
sunscreen with a broad spectrum SPF of 15 or higher and other sun protection
measures including: • Limit time in sun, especially from 10 a.m. - 2 p.m. • Wear
long-sleeve shirts, pants, hats, and sunglasses. • Children under six months of age:
Ask a doctor.

Inactive ingredients

Petrolatum, Ozokerite, Mineral Oil, Cocoa Butter, Beeswax,
Isopropyl Isostearate, Hydrogenated Castor Oil, Microcrystalline Wax, Olivate,
Fragrance, Vitamin E.